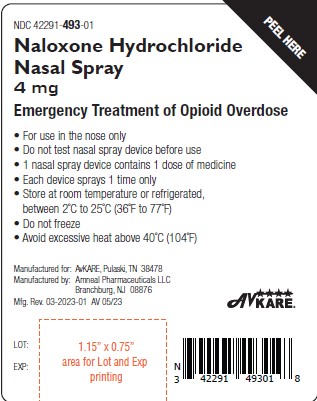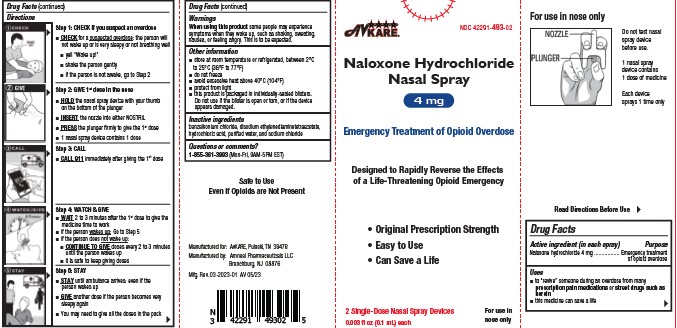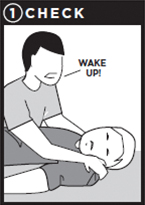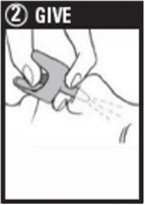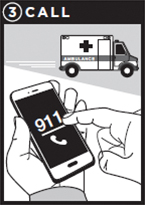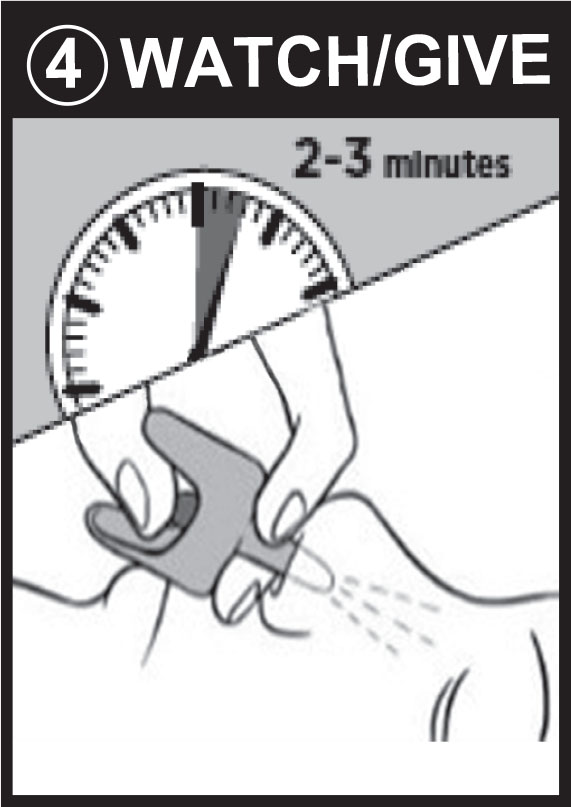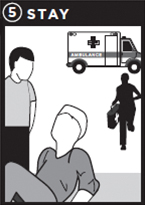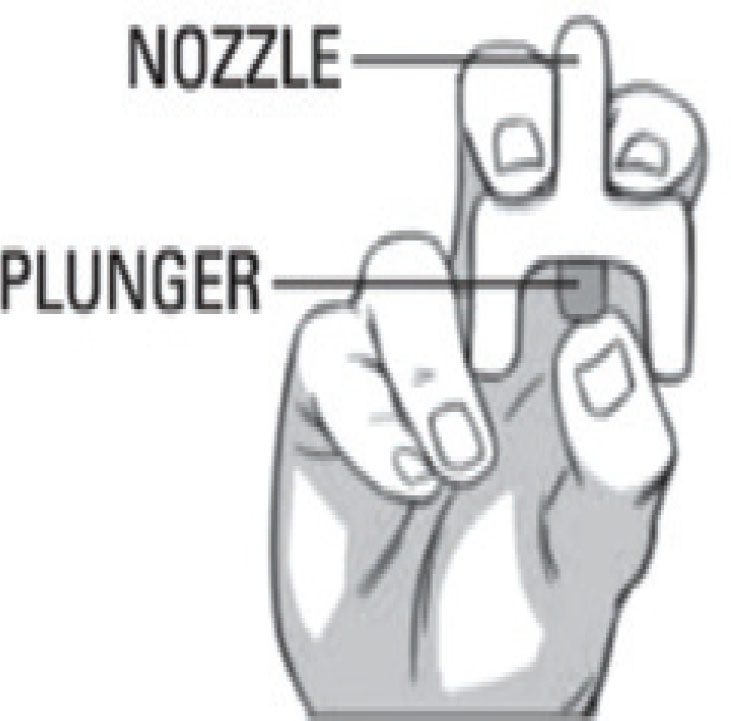 DRUG LABEL: Naloxone Hydrochloride
NDC: 42291-493 | Form: SPRAY
Manufacturer: AvKARE
Category: otc | Type: HUMAN OTC DRUG LABEL
Date: 20260114

ACTIVE INGREDIENTS: NALOXONE HYDROCHLORIDE 4 mg/0.1 mL
INACTIVE INGREDIENTS: BENZALKONIUM CHLORIDE; EDETATE DISODIUM; SODIUM CHLORIDE; WATER; HYDROCHLORIC ACID

Naloxone Hydrochloride Nasal Spray

Active ingredient (in each spray)

Naloxone hydrochloride 4 mg

Purpose

Emergency treatment of opioid overdose

Use(s)

- to “revive” someone during an overdose from many prescription pain medicationsor street drugs such as heroin
- this medicine can save a life

Warnings

When using this product

some people may experience symptoms when they wake up, such as shaking, sweating, nausea, or feeling angry. This is to be expected.

Directions

Step 1: CHECK if you suspect an overdose

- CHECKfor a suspected overdose: the person will not wake up or is very sleepy or not breathing well
- yell “Wake up!”
- shake the person gently
- if the person is not awake, go to Step 2

Step 2: GIVE 1st dose in the nose

- HOLDthe nasal spray device with your thumb on the bottom of the plunger
- INSERTthe nozzle into either NOSTRIL
- PRESSthe plunger firmly to give the 1st dose
- 1 nasal spray device contains 1 dose

Step 3: CALL 911

- CALL 911immediately after giving the 1st dose

Step 4: WATCH & GIVE

- WAIT2 to 3 minutes after the 1st dose to give the medicine time to work
- if the person wakes up: Go to Step 5
- if the person does not wake up:
- CONTINUE TO GIVEdoses every 2 to 3 minutes until the person wakes up
- it is safe to keep giving doses

Step 5: STAY

- STAYuntil ambulance arrives: even if the person wakes up
- GIVEanother dose if the person becomes very sleepy again
- You may need to give all the doses in the pack

Other information

- store at room temperature or refrigerated, between 2°C to 25°C (36°F to 77°F)
- do not freeze
- avoid excessive heat above 40°C (104°F)
- protect from light
- this product is packaged in individually-sealed blisters. Do not use if the blister is open or torn, or if the device appears damaged.

Inactive ingredients

benzalkonium chloride, disodium ethylenediaminetetraacetate, hydrochloric acid, purified water, and sodium chloride

DIRECTIONS

Naloxone Hydrochloride Nasal Spray, 4 mg

Emergency Treatment of Opioid Overdose

Important:

- For use in the nose only
- Do not test nasal spray device before use
- 1 nasal spray device contains 1 dose of medicine
- Each device sprays 1 time only

Step 1: CHECK if you suspect an overdose

- CHECK for a suspected overdose: the person will not wake up or is very sleepy or not breathing well
- yell “Wake up!”
- shake the person gently
- if the person is not awake, go to Step 2

Step 2: GIVE 1st dose in the nose

- HOLD the nasal spray device with your thumb on the bottom of the plunger
- INSERT the nozzle into either NOSTRIL
- PRESS the plunger firmly to give the 1st dose
- 1 nasal spray device contains 1 dose

Step 3: CALL 911

- CALL 911 immediately after giving the 1st dose

Step 4: WATCH & GIVE

- WAIT 2 to 3 minutes after the 1st dose to give the medicine time to work
- if the person wakes up: Go to Step 5
- if the person does not wake up:
- CONTINUE TO GIVE doses every 2 to 3 minutes until the person wakes up
- it is safe to keep giving doses

Step 5: STAY

- STAY until ambulance arrives: even if the person wakes up
- GIVE another dose if the person becomes very sleepy again
- You may need to give all the doses in the pack

For opioid emergencies, call 911.For questions or more information about Naloxone Hydrochloride Nasal Spray, contact

AvKARE at 1-855-361-3993.

Mfg. Rev. 03-2023-01 AV 05/23